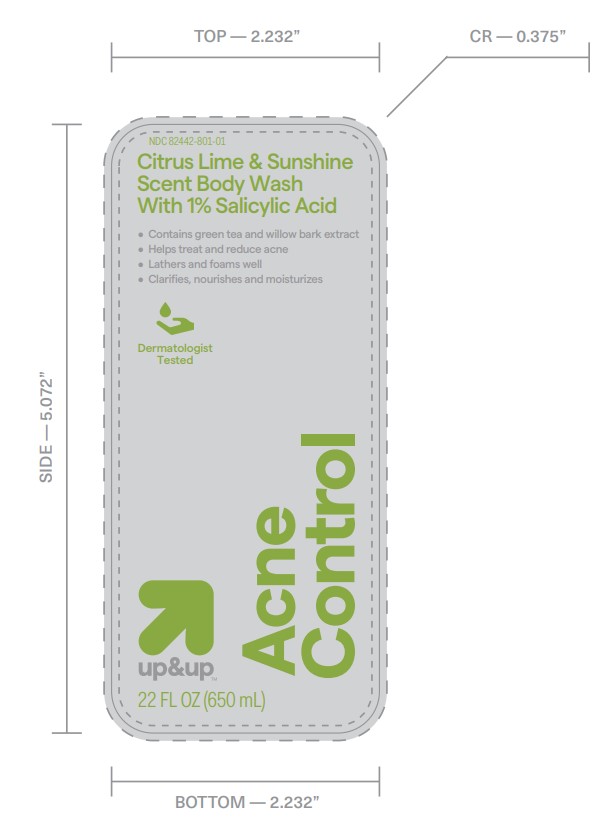 DRUG LABEL: Acne Wash
NDC: 82442-805 | Form: LIQUID
Manufacturer: Target Corporation
Category: otc | Type: HUMAN OTC DRUG LABEL
Date: 20251018

ACTIVE INGREDIENTS: SALICYLIC ACID 1 mg/100 mg
INACTIVE INGREDIENTS: TETRASODIUM GLUTAMATE DIACETATE 1 mg/100 mg; GLUCONOLACTONE 1 mg/100 mg; DECYL GLUCOSIDE 0.5 mg/100 mg; FRAGRANCE 13576 0.7 mg/100 mg; COCAMIDOPROPYL BETAINE 0.05 mg/100 mg; SODIUM BENZOATE 1 mg/100 mg; CAMELLIA SINENSIS SEED OIL 0.05 mg/100 mg; WILLOW BARK 0.05 mg/100 mg; WATER 77.65 mg/100 mg; PEG-120 METHYL GLUCOSE DIOLEATE 1 mg/100 mg; GLYCERIN 4 mg/100 mg; SODIUM C14-16 OLEFIN SULFONATE 4 mg/100 mg

Target Acne Wash (22 Fl. Oz .)

Active Ingredient

Active Ingredient Purpose

Salicylic Acid 1% w/v

USE

For the treatment of acne.

When using this product

skin irritaion and dryness is more likely to occur if you use another topical acne medication at the same time. If irritation occurs, only use one topical medication at a time.

Directions

- Generously lather on body. For maximum lather, use a netted sponge or washcloth. Rinse thoroughly.
- Avoid conttact with eyes. If contact occurs, flush thoroughly with water.

In active Ingredients

Wate, Cocamidopropyl Betaine, Vegetable Glycerin, Sodium C14-C16 Olefin Sulfonate, PEG-120 Methyl Glucose Dioleate, Fragrance, Decyl Gliucoside, Salix Alba (Willow) Bark Extract, Camellia Sinensis Leaf Extract, Tetrasodium Glutamate Diacetate, Gluconolactone, Sodium Benzoate.

Distributed By: Target Corporation: Questions or Comments

Distributed By:Target Corporation

Minneapolis, MN 55403

Questions or comments? Call 1-800-910-6874

ORIGIN: USA WITH GLOBALLY SOURCED MATERIALS

Keep out of Reach of Children. If swallowed , get medical help or contact a Poison Control Center right away.

Purpose

Acne Medication

Store at Room Temperature

WARNING

For External Use Only

PRINCIPLE DISPLAY PANEL

Citrus Lime & Sunshine Scent Body Wash with 1% Salicylic Acid

Contains green tea and willow bark extract

Helps treat and reduce acne

Lathers and foams well

clarifies, nourishes and moissturizes

Dermatologist Tested

up &up Acne Control

NDC 82442-801-01

22 fl. oz (6565 mL)